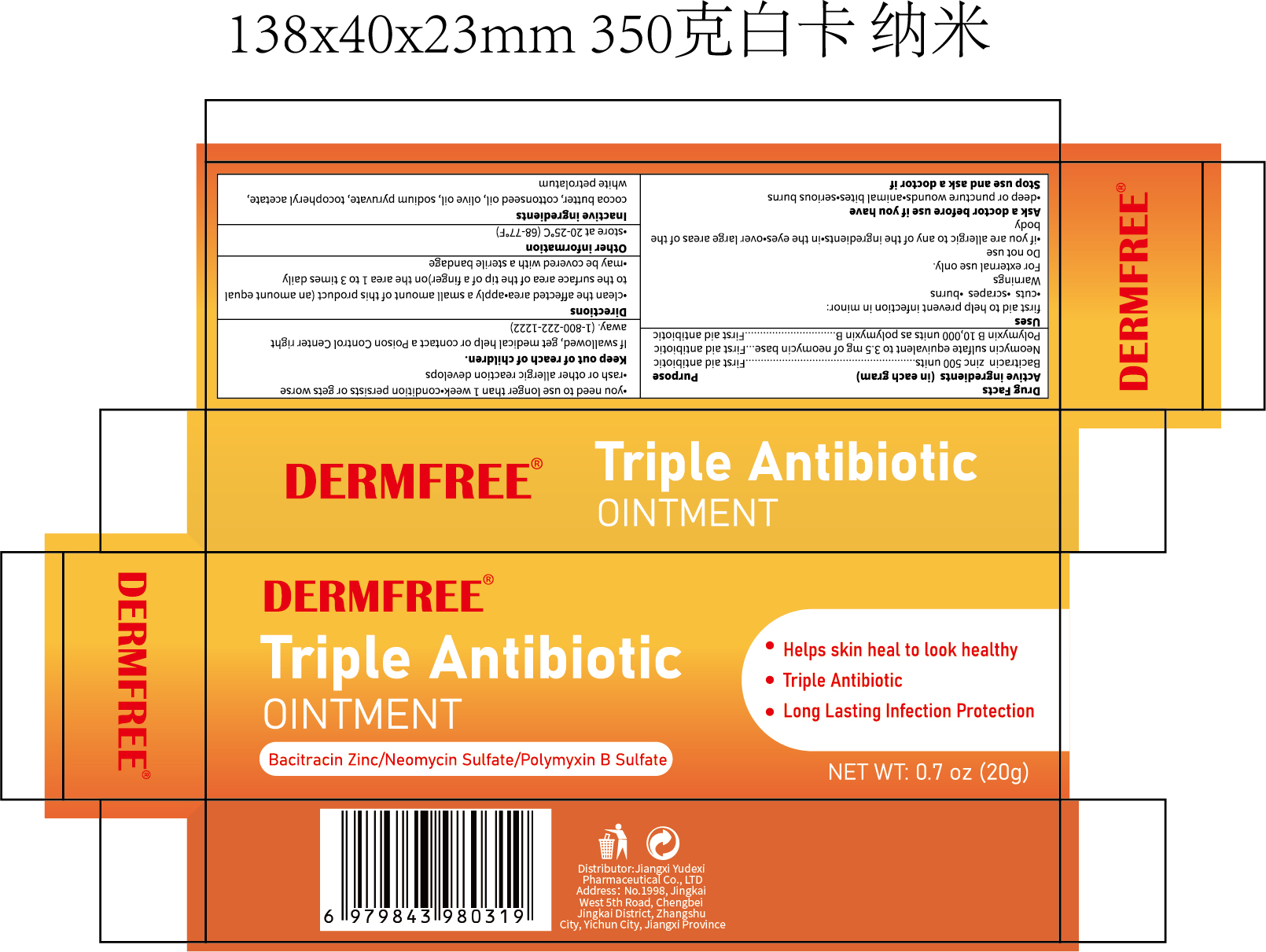 DRUG LABEL: DERMFREE Triple Antibiotic
NDC: 85248-117 | Form: OINTMENT
Manufacturer: Jiangxi Yudexi Pharmaceutical Co., LTD
Category: otc | Type: HUMAN OTC DRUG LABEL
Date: 20260208

ACTIVE INGREDIENTS: NEOMYCIN SULFATE 3.5 mg/1 g; POLYMYXIN B 10000 [USP'U]/1 g; BACITRACIN ZINC 500 [USP'U]/1 g
INACTIVE INGREDIENTS: OLIVE OIL; .ALPHA.-TOCOPHEROL ACETATE; WHITE PETROLATUM; SODIUM PYRUVATE; COCOA BUTTER

85248-117

Active Ingredient

Bacitracin zinc 500 units
Neomycin sulfate equivalent to 3.5 mg of neomycin base Polymyxin B 10,000 units as polymyxin B sulfate

Purpose

First aid antibiotic

Use

first aid to help prevent infection in minor: .cuts .scrapes .burns

Warnings

For external use only.

Do not use

.if you are allergic to any of the ingredients .in the eyes .over large areas of the body

When Using

Ask a doctor before use if you have .deep or puncture wounds .animal bites .serious burns

Stop Use

.you need to use longer than l week .condition persists or gets worse .rash or other allergic reaction develops

Ask Doctor

.deep or puncture wounds .animal bites .serious burns

Keep Oot Of Reach Of Children

If swallowed, get medical help or contact a Poison Control Center right away.(1-800-222-1222)

Directions

.clean the affected area .apply a small amount of this product (an amount equalto the surface area of the tip of a finger)on the area l to 3 times daily .may be covered with a sterile bandage

Other information

store at 20-25°C(68-77°F)

Inactive ingredients

cocoa butter, cottonseed oil, olive oil, sodium pyruvate, tocopheryl acetate.white petrolatum